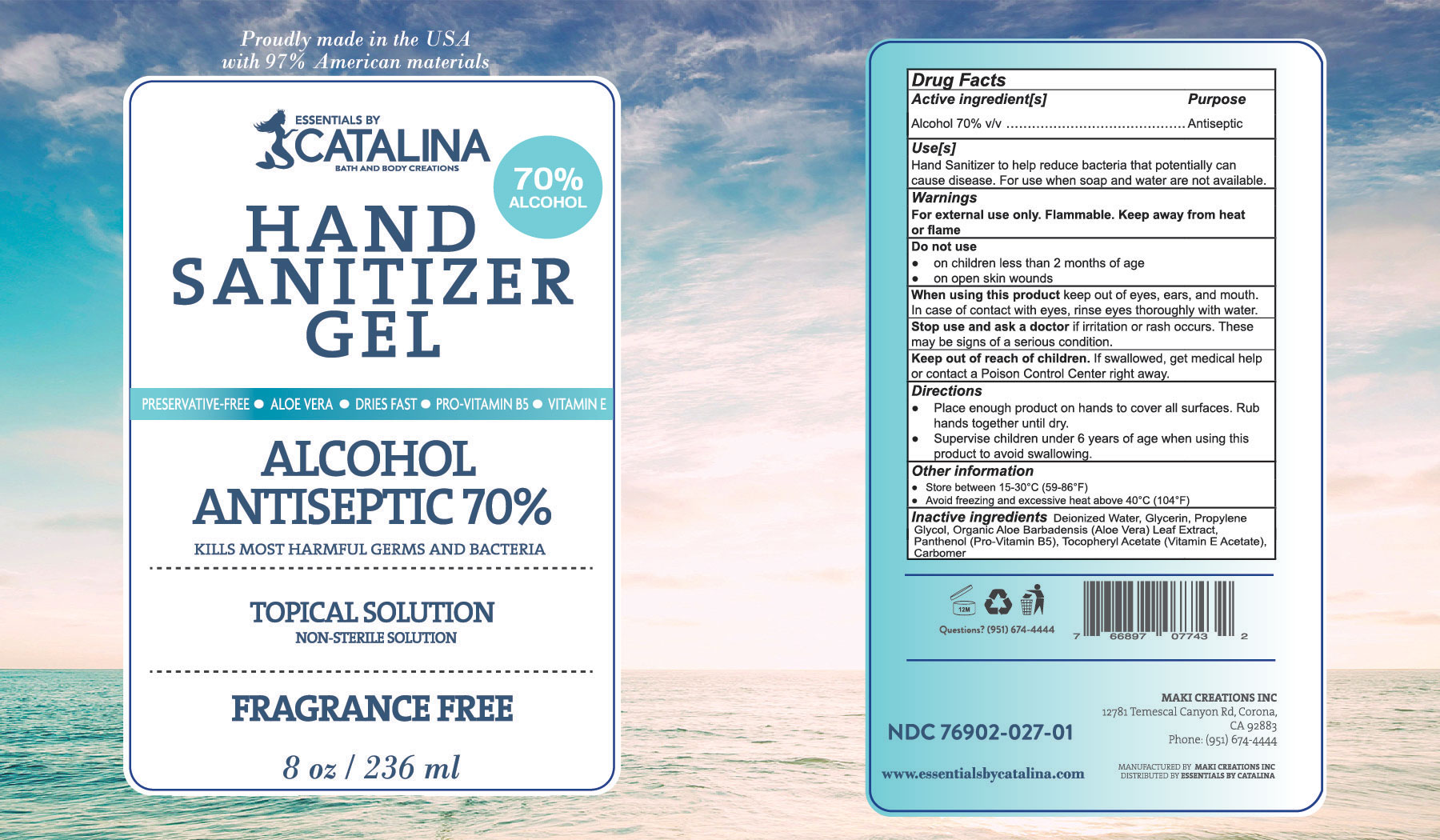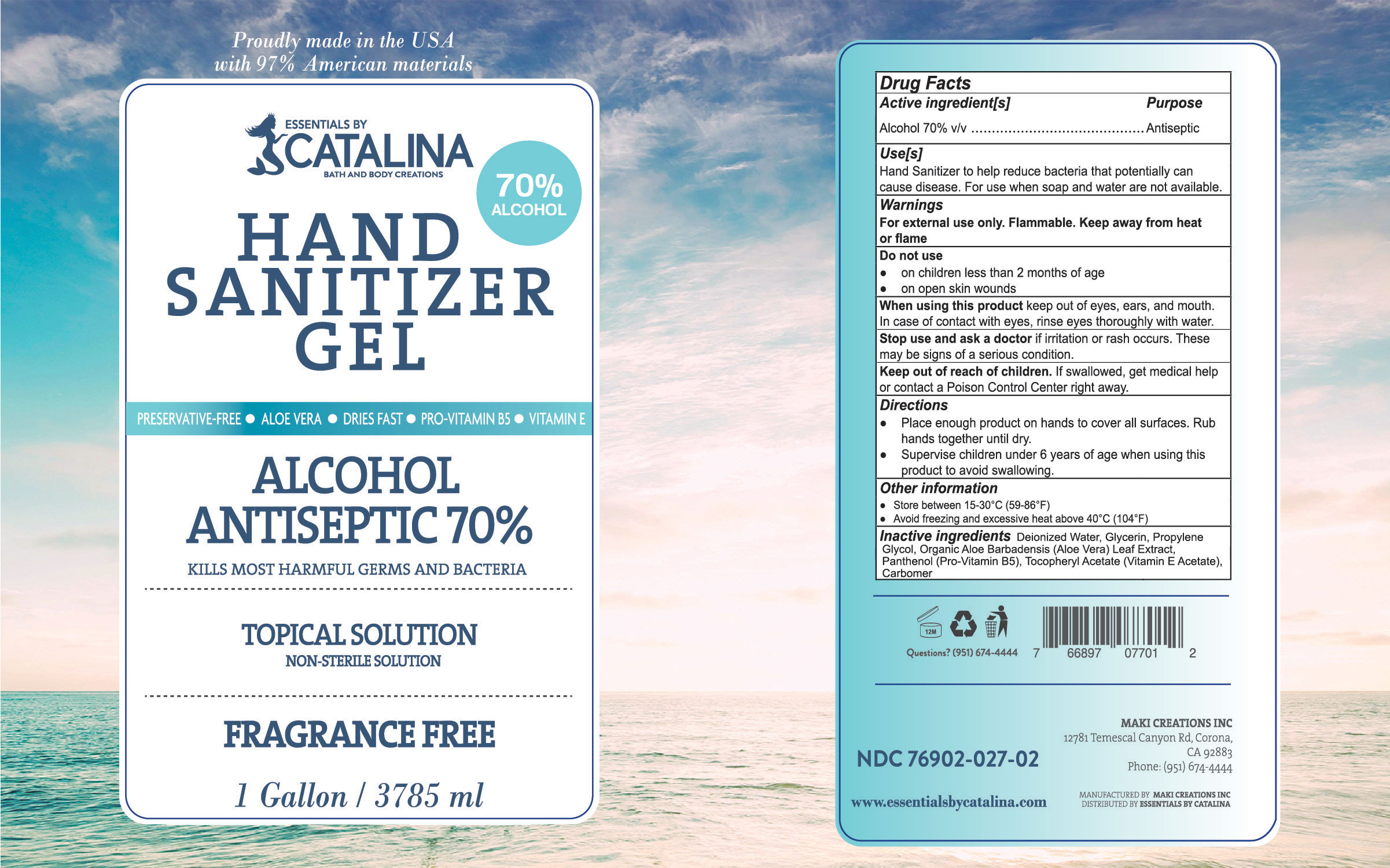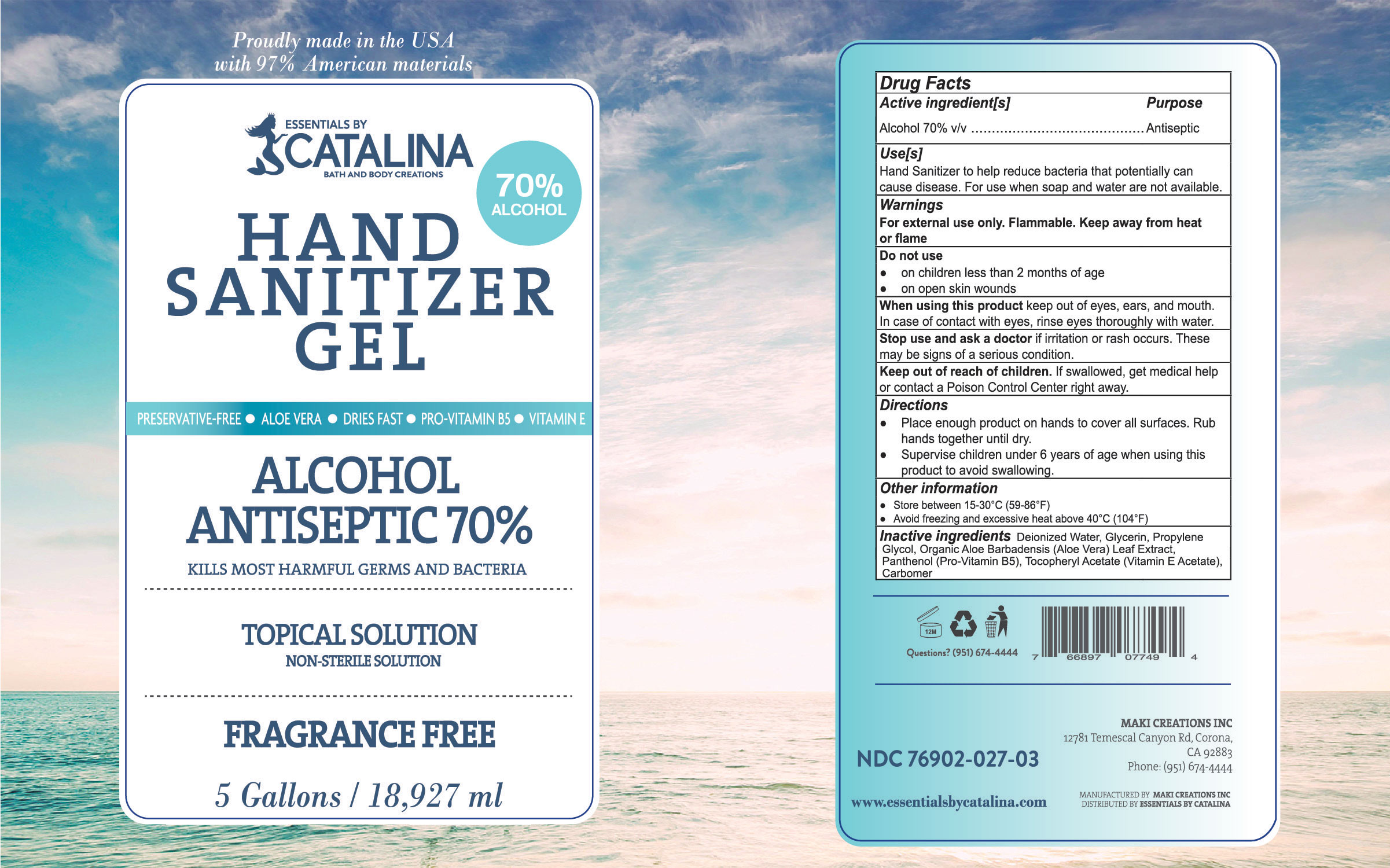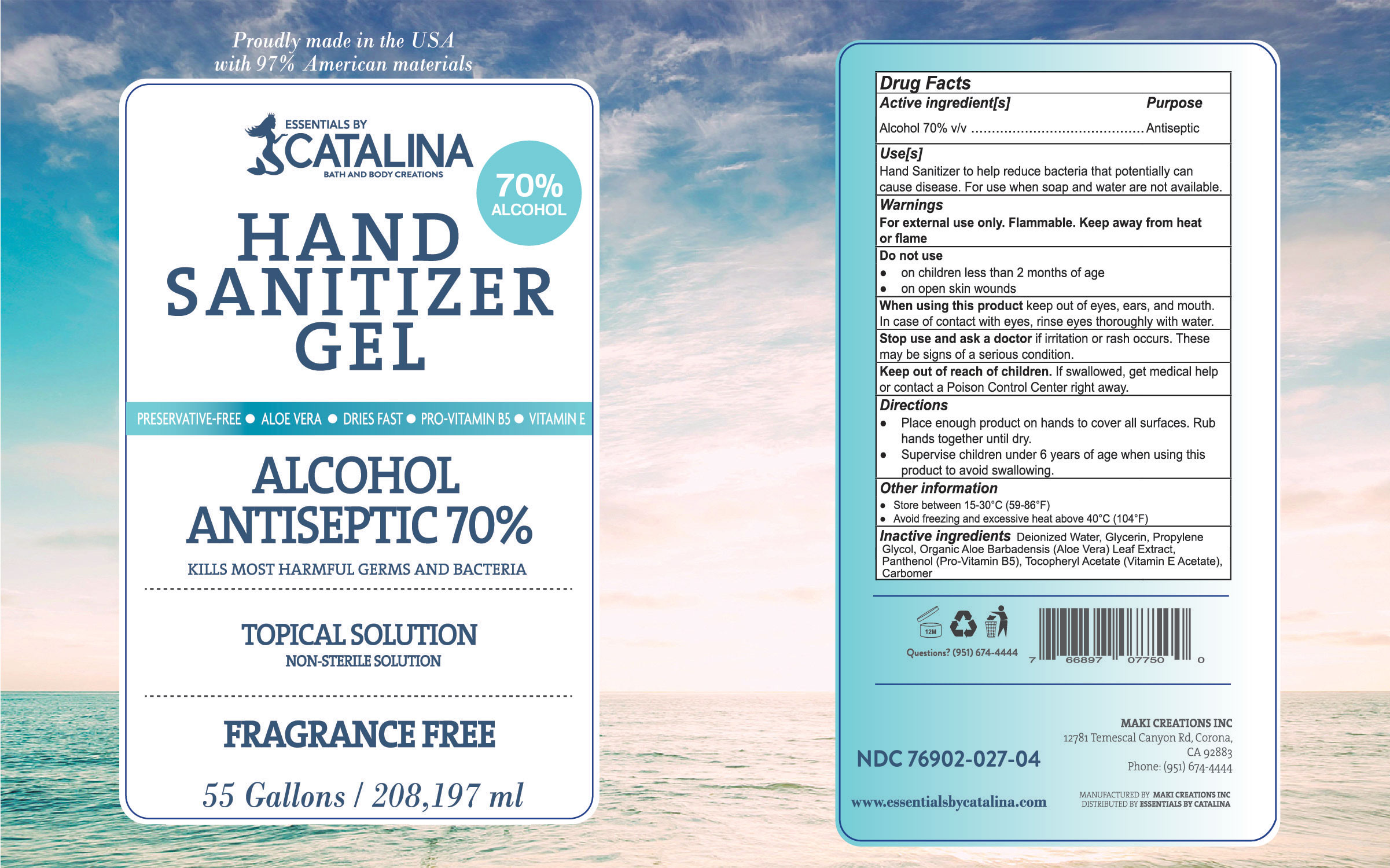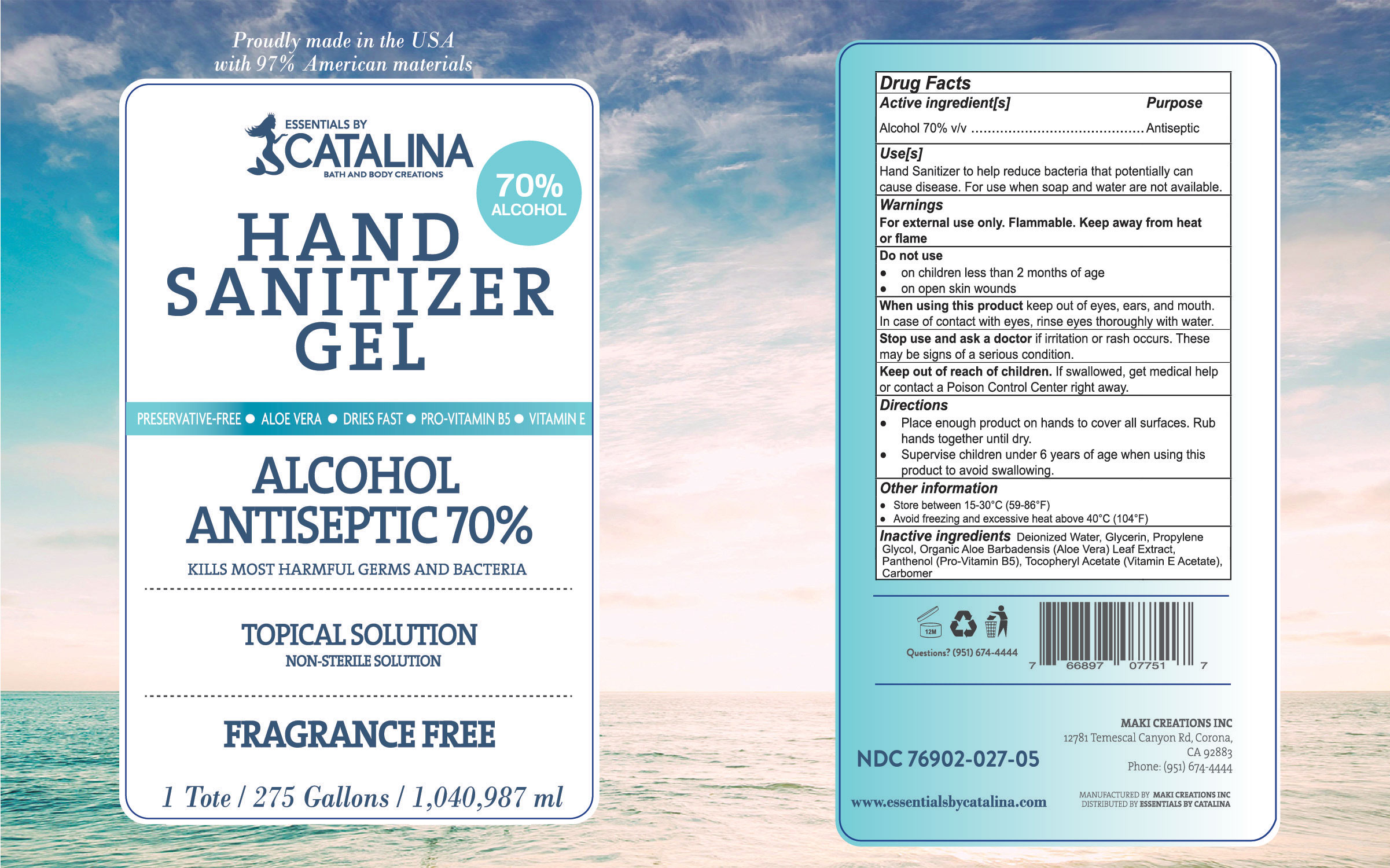 DRUG LABEL: Essentials by Catalina Hand Sanitizer Gel
NDC: 76902-027 | Form: LIQUID
Manufacturer: Maki Creations
Category: otc | Type: HUMAN OTC DRUG LABEL
Date: 20200604

ACTIVE INGREDIENTS: ALCOHOL 70 mL/100 mL
INACTIVE INGREDIENTS: WATER 25.852 mL/100 mL; PROPYLENE GLYCOL 0.841 mL/100 mL; GLYCERIN 1.381 mL/100 mL; PANTHENOL 0.007 mL/100 mL; .ALPHA.-TOCOPHEROL ACETATE, D- 0.009 mL/100 mL; AMINOMETHYLPROPANOL 0.373 mL/100 mL; ALOE VERA LEAF 0.009 g/100 mL; CARBOMER 940 1.515 mL/100 mL

Essentials by Catalina Hand Sanitizer Gel

Active Ingredient[s]

Alcohol 80% v/v

Purpose

Antiseptic

Uses[s]

Hand Sanitizer to help reduce bacteria that potentially can cause disease. For use when soap and water are not available.

Warnings

For external use only. Flammable. Keep away from heat or flame.

Do not use

- on children less than 2 months of age
- on open skin wounds

When using this product keep out of eyes, ears, and mouth. In case of contact with eyes, rinse eyes thoroughly with water.

Stop use and ask a doctor if irritation or rash occurs. These may be signs of a serious condition.

Keep out of reach of children. If swallowed, get medical help or contact a Poison Center right away.

Directions

- Place enough product on hands to cover all surfaces. Rub hands together until dry.
- Supervise children under 6 years of age when using this product to avoid swallowing.

Other information

- Store between 15-30°C (59-86°F)
- Avoid freezing and excessive heat above 40°C (104°F)

Inactive Ingredients

Deionized Water, Glycerin, Propylene Glycol, Organic Aloe Barbadensis (Aloe Vera) Leaf Extract, Panthenol (Pro-Vitamin B5), Tocopheryl Acetate (Vitamin E Acetate), Carbomer, Aminomethyl Propanol